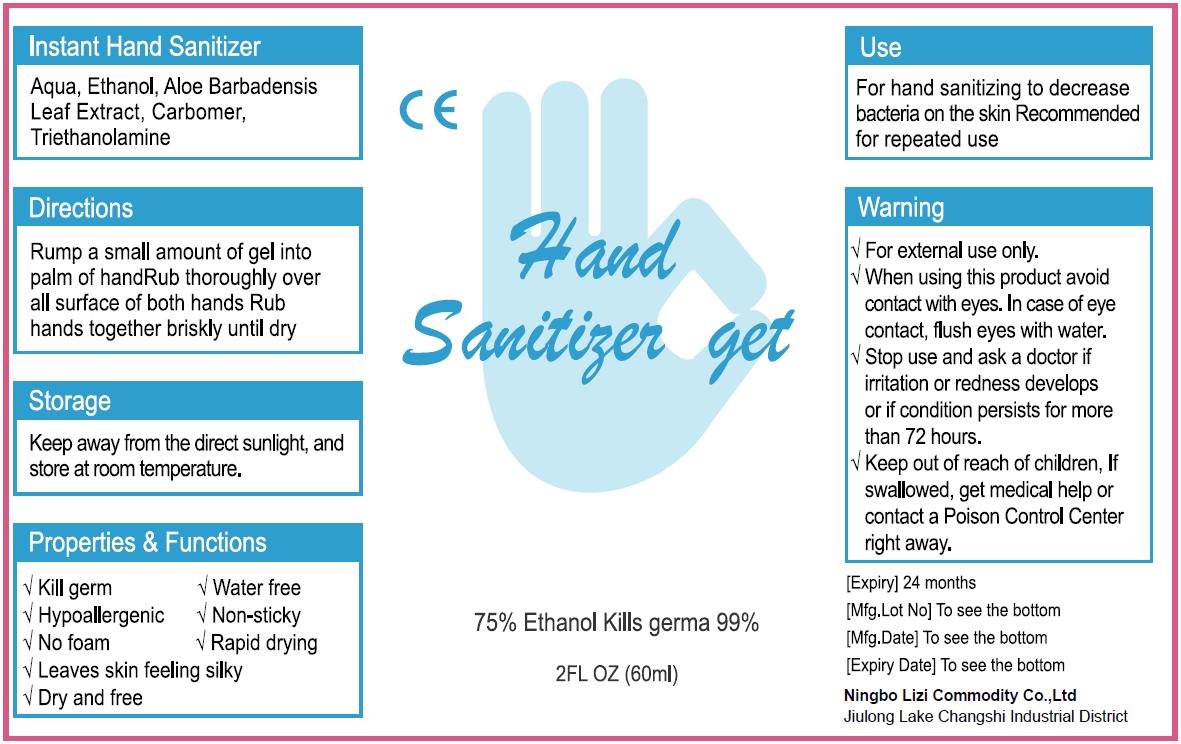 DRUG LABEL: Hand Sanitizer
NDC: 75329-2011 | Form: GEL
Manufacturer: Ningbo Lizi Commodity Co., Ltd.
Category: otc | Type: HUMAN OTC DRUG LABEL
Date: 20200619

ACTIVE INGREDIENTS: ALCOHOL 45 mL/60 mL
INACTIVE INGREDIENTS: ALOE VERA LEAF; CARBOMER HOMOPOLYMER, UNSPECIFIED TYPE; WATER; TROLAMINE

LiZi, Hand Sanitizer, Gel, 75% Ethanol, 60mL

Active Ingredient(s)

Alcohol 75% v/v. Purpose: Antiseptic

Purpose

Antiseptic, Hand Sanitizer

Use

Hand Sanitizer to help reduce bacteria that potentially can cause disease. For use when soap and water are not available.

Warnings

For external use only. Flammable. Keep away from heat or flame

Do not use

- in children less than 2 months of age
- on open skin wounds

When using this product keep out of eyes, ears, and mouth. In case of contact with eyes, rinse eyes thoroughly with water.
Stop use and ask a doctor if irritation or rash occurs. These may be signs of a serious condition.
Keep out of reach of children. If swallowed, get medical help or contact a Poison Control Center right away.

Stop use and ask a doctor if irritation or rash occurs. These may be signs of a serious condition.

Keep out of reach of children. If swallowed, get medical help or contact a Poison Control Center right away.

Directions

- Place enough product on hands to cover all surfaces. Rub hands together until dry.
- Supervise children under 6 years of age when using this product to avoid swallowing.

Other information

Keep away from the direct sunlight, and store at room temperature.

Inactive ingredients

Aqua, Aloe Barbadense Leaf Extract, Carbomer, Triethanolamine